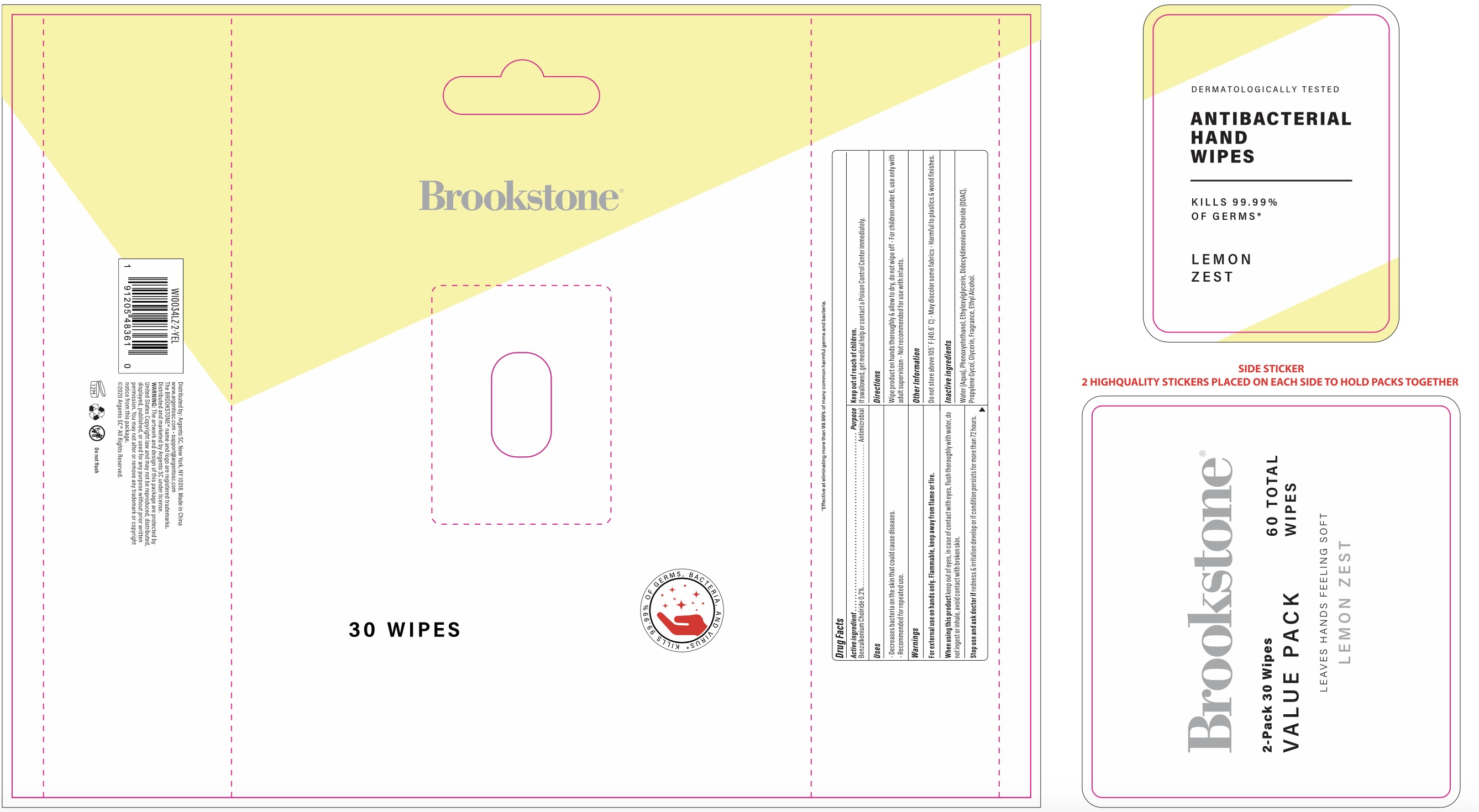 DRUG LABEL: Brookstone Value Pack Antibacterial Hand Wipes Lemon Zest
NDC: 77731-080 | Form: SOLUTION
Manufacturer: Argento sc by sicura inc.
Category: otc | Type: HUMAN OTC DRUG LABEL
Date: 20200903

ACTIVE INGREDIENTS: BENZALKONIUM CHLORIDE 0.006 g/1 1
INACTIVE INGREDIENTS: ETHYLHEXYLGLYCERIN; PROPYLENE GLYCOL; WATER; PHENOXYETHANOL; DIDECYLDIMONIUM CHLORIDE; GLYCERIN; ALCOHOL

WI0034LZ-2-YEL

Active Ingredient(s)

Benzalkonium Chloride 0.2%

Purpose:

Antimicrobial

USE

Decrease bacteria on skin that could cause diseases

Recommended for repeated use

warnings

For external use only on hands. Flammable, keep way from flame or fire

When using this product, keep out of eyes. In case of contact with eyes, flush thoroughly with water

Do not ingest or inhale

Avoid contact with broken skin

Stop use and ask a doctor

if redness and irritation develop and or condition persists for more than 72 hours

keep out of reach of children

if swallowed,get medical help or contact a Poison Control Center immediately

Directions

- Wipe product on hands thoroughly and allow to dry, do not wipe off
- For children under 6, use only with adult supervision
- Not recommended for use with infants

other information

Do not store above 105F (40.6C)

May discolor some fabrics

Harmful to plastics and wood finishes

inactive ingredients

Water, Phenoxyethanol, Ethylhexylglycerin, Didecyldimonium Chloride, Propylene Glycol, Glycerin, Fragrance, Ethyl Alcohol